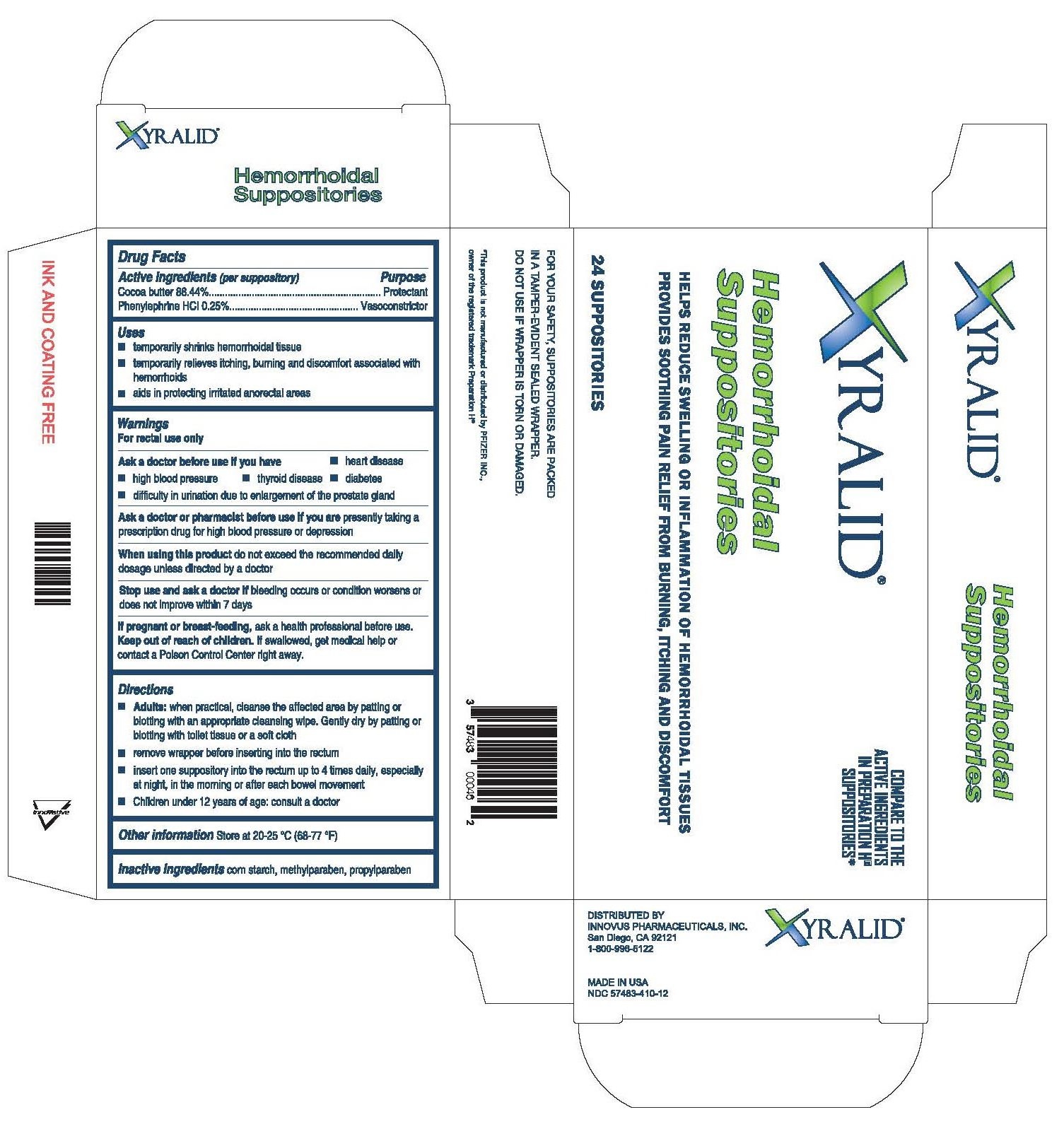 DRUG LABEL: Xyralid Hemorrhoidal
NDC: 57483-410 | Form: SUPPOSITORY
Manufacturer: Innovus Pharmaceuticals, Inc.
Category: otc | Type: HUMAN OTC DRUG LABEL
Date: 20180503

ACTIVE INGREDIENTS: COCOA BUTTER 88.5 g/100 g; PHENYLEPHRINE HYDROCHLORIDE 0.26 g/100 g
INACTIVE INGREDIENTS: METHYLPARABEN 0.02 g/100 g; PROPYLPARABEN 0.02 g/100 g; MODIFIED CORN STARCH (1-OCTENYL SUCCINIC ANHYDRIDE) 11.2 g/100 g

Active ingredients

Active Ingredients Purpose

Cocoa butter 88.50%...................................................................Protectant

Phenylephrine hydrochloride 0.26%..............................................Vasoconstrictor

Uses

- temporarily shrinks hemorrhoidal tissue
- temporarily relieves itching, burning, and discomfort associated with hemorrhoids
- aids in protecting irritated anorectal areas

Warnings

For rectal use only

Ask a doctor or pharmacist before use if you are presently taking a prescription drug for high blood pressure or depression

Ask a doctor before use if you have

-heart disease -high blood pressure

-thyroid disease -diabetes

-difficulty in urination due to enlargement of the prostate gland

When using this product

do not exceed the recommended daily dosage unless directed by a doctor

Stop use and ask a doctor if

bleeding occurs or condition worsens or does not improve within 7 days

If pregnant or breastfeeding

ask a health professional before use.

Keep out of reach of children. If swallowed, get medical help or contact a Poison Control Center right away.

Directions

-Adults: when practical, cleanse the affected area by patting or blotting with an appropriate cleansing wipe. Gently dry by patting or blotting with a toilet tissue or a soft cloth.

-remove the wrapper before inserting into the rectum.

-insert one suppository into the rectum up to 4 times daily, especially at night, in the morning or after each bowel movement.

-Children under 12 years of age: consult a doctor

Other information

Store at 20-25oC (68-77oF)

Inactive ingredients

corn starch, methylparaben, propylparaben

Purpose

Protectant

Vasoconstrictor